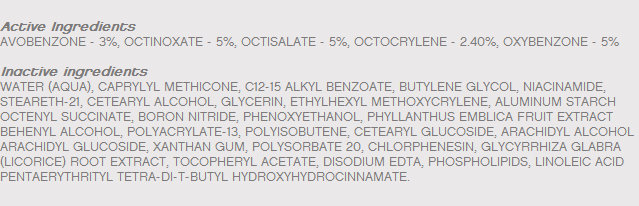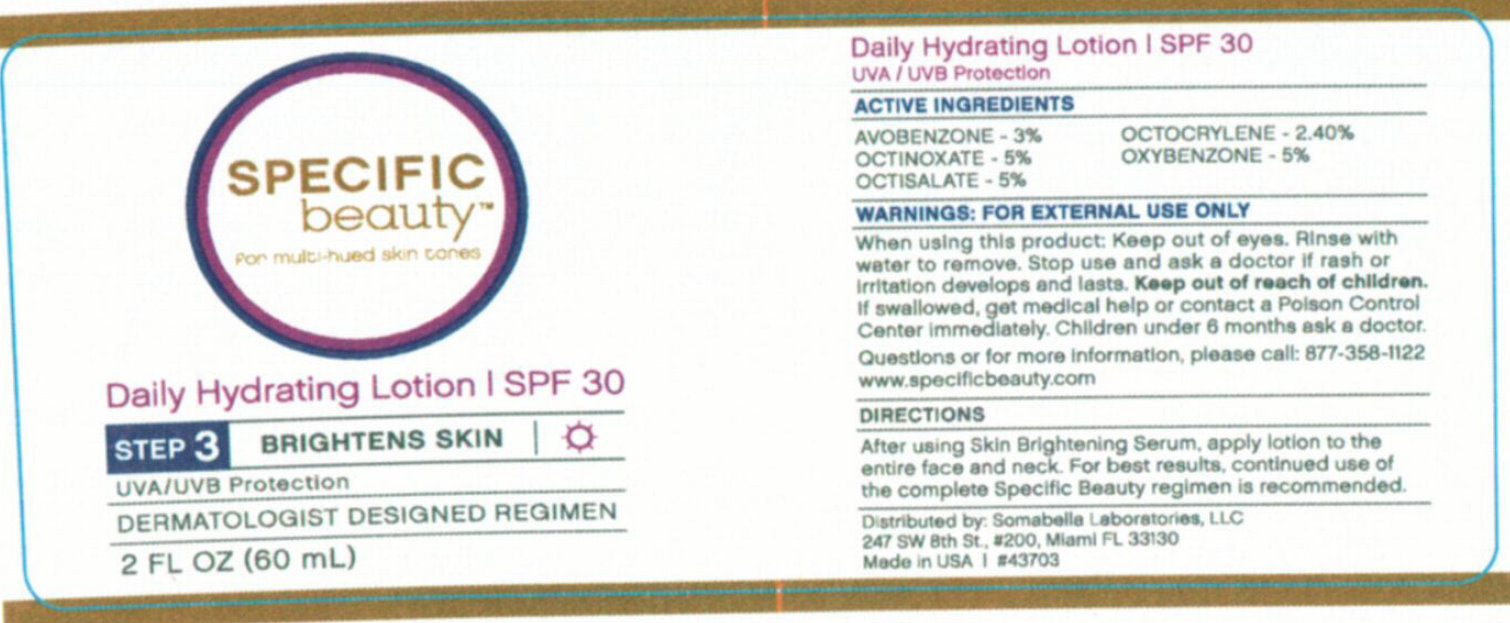 DRUG LABEL: SPECIFIC BEAUTY DAILY HYDRATING SPF 30
NDC: 52295-200 | Form: LOTION
Manufacturer: Somabella Laboratories, LLC
Category: otc | Type: HUMAN OTC DRUG LABEL
Date: 20190404

ACTIVE INGREDIENTS: AVOBENZONE 30 mg/1 mL; OCTOCRYLENE 24 mg/1 mL; OCTINOXATE 50 mg/1 mL; OXYBENZONE 50 mg/1 mL; OCTISALATE 50 mg/1 mL
INACTIVE INGREDIENTS: WATER; MYRISTYL TRISILOXANE; ALKYL (C12-15) BENZOATE; BUTYLENE GLYCOL; NIACINAMIDE; STEARETH-21; CETOSTEARYL ALCOHOL; GLYCERIN; ALUMINUM STARCH OCTENYLSUCCINATE; PHENOXYETHANOL; DOCOSANOL; CETEARYL GLUCOSIDE; ARACHIDYL ALCOHOL; XANTHAN GUM; POLYSORBATE 20; CHLORPHENESIN; GLYCYRRHIZA GLABRA; ALPHA-TOCOPHEROL ACETATE; EDETATE DISODIUM; LINOLEIC ACID

SPECIFIC BEAUTY DAILY HYDRATING LOTION SPF 30

ACTIVE INGREDIENTS

AVOBENZONE - 3 percent

OCTOCRYLENE - 2.4 percent

OCTINOXATE - 5 percent

OXYBENZONE - 5 percent

OCTISALATE - 5 percent

WARNINGS: FOR EXTERNAL USE ONLY

When using this product: Keep out of eyes, Rinse with water to remove.

Stop use and ask a doctor if rash or irritation develops and lasts.

Keep out of reach of children: If swallowed, get medical help or contact a Poison Control Center immediately

DOSAGE AND ADMINISTRATION

Children under 6 months ask a doctor.

After using Skin Brightening Serum, apply lotion to the entire face and neck. For best results, continued use of the complete Specific Beauty regimen is recommended.

DESCRIPTION

Questions or for more information, please call: 877-358-1122

www.specificbeauty.com

Distributed by: Somabella Laboratories, LLC

247 SW ith St., #200, Miami FL 33130

Made in USA #43703

Inactive Ingredients

WATER (AQUA), CAPRYLYL METHICONE, C12-15 ALKYL BENZOATE, BUTYLENE GLYCOL, NIACINAMIDE, STEARETH-21, CETEARYL ALCOHOL, GLYCERIN, ETHYLHEXYL METHOXYCRYLENE, ALUMINUM STARCH OCTENYL SUCCINATE, BORON NITRIDE, PHENOXYETHANOL, PHYLLANTHUS EMBLICA FRUIT EXTRACT BEHENYL ALCOHOL, POLYACRYLATE-13, POLYISOBUTENE, CETEARYL GLUCOSIDE, ARACHIDYL ALCOHOL ARACHIDYL GLUCOSIDE, XANTHAN GUM, POLYSORBATE 20,
CHLORPHENESIN, GLYCYRRHIZA GLABRA (LICORICE) ROOT EXTRACT, TOCOPHERYL ACETATE, DISODIUM EDTA, PHOSPHOLIPIDS, LINOLEIC ACID PENTAERYTHRITYL TETRA-DI-T-BUTYL HYDROXYHYDROCINNAMATE.

PACKAGE LABEL

SPECIFIC beauty For multi-hued skin tones
Daily Hydrating Lotion; SPF 30
STEP 3 BRIGHTENS SKIN
UVA/UVB Protection
DERMATOLOGIST DESIGNED REGIMEN
2 FL OZ (60 mL)